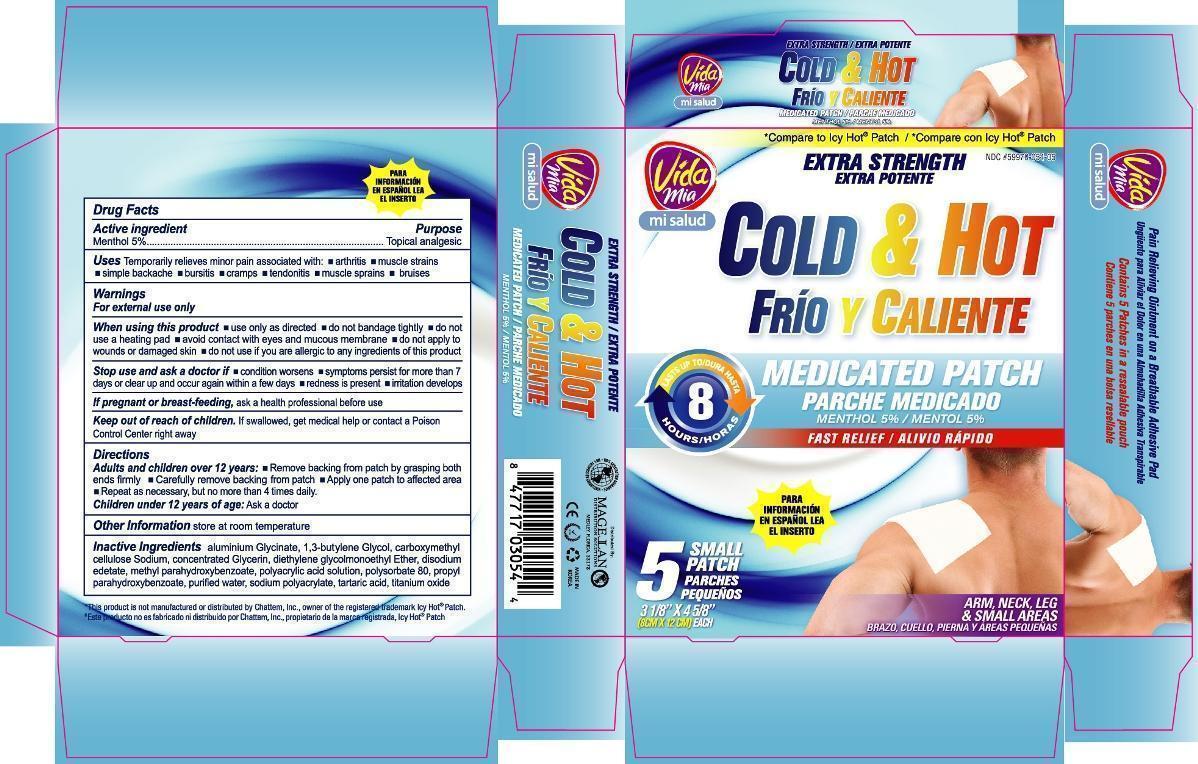 DRUG LABEL: Cold and Hot Pain Relief
NDC: 59970-054 | Form: PATCH
Manufacturer: Navarro Discount Pharmacies,LLC
Category: otc | Type: HUMAN OTC DRUG LABEL
Date: 20120801

ACTIVE INGREDIENTS: MENTHOL 400 mg/1 1
INACTIVE INGREDIENTS: DIHYDROXYALUMINUM AMINOACETATE; BUTYLENE GLYCOL; CARBOXYMETHYLCELLULOSE SODIUM; GLYCERIN; DIETHYLENE GLYCOL MONOETHYL ETHER; EDETATE DISODIUM; METHYLPARABEN; POLYSORBATE 80; PROPYLPARABEN; WATER; TARTARIC ACID; TITANIUM DIOXIDE

Drug Facts

Active Ingredient

Menthol 5%

Purpose

Topical analgesic

Uses

Temporarily relieves minor pain associated with:

- arthritis
- muscle strains
- simple backache
- bursitis
- cramps
- tendonitis
- muscle sprains
- bruises

Warnings

For external use only

When using this product

- use only as directed
- do not bandage tightly
- do not use a heating pad
- avoid contact with eyes and mucous membrane
- do not apply to wounds or damaged skin
- do not use if you are allergic to any ingredients of this product

Stop use and ask a doctor if

- condition worsens
- symptoms persist for more than 7 days or clear up and occur again within a few days
- redness is present
- irritation develops

If pregnant or breast-feeding,

ask a health professional before use.

Keep out of reach of children.

If swallowed, get medical help or contact a Poison Control Center right away.

Directions

Adults and children over 12 years:

- Remove backing from patch by grasping both ends firmly
- Carefully remove backing from patch
- Apply one patch to affected area
- Repeat as necessary, but no more than 4 times daily

Children under 12 years of age: Ask a doctor

Other information

store at room temperature

Inactive ingredients

aluminium glycinate, 1,3-butylene glycol, carboxymethylcellulose sodium, concentrated glycerin, diethylene glycol monoethyl ether, disodium edetate, methyl parahydroxybenzoate, polyacrylic acid solution, polysorbate 80, propyl parahydroxybenzoate, purified water, tartaric acid, titanium dioxide

package label

Cold and Hot Pain Relief Patch